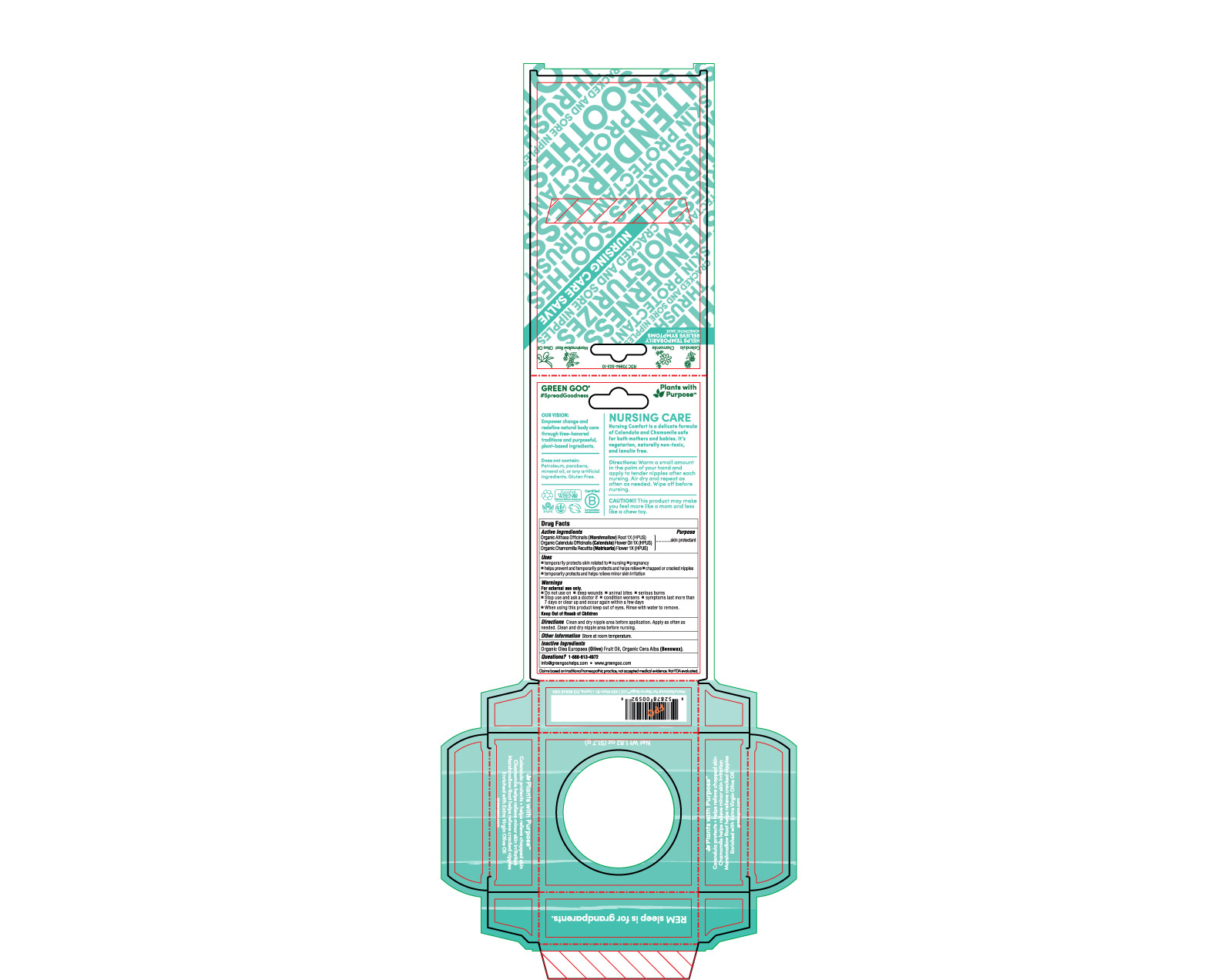 DRUG LABEL: Nursing Cream
NDC: 70994-503 | Form: SALVE
Manufacturer: Spry Life LLC
Category: homeopathic | Type: HUMAN OTC DRUG LABEL
Date: 20251215

ACTIVE INGREDIENTS: ALTHAEA OFFICINALIS ROOT 1 [hp_X]/51.7 g; CALENDULA OFFICINALIS FLOWER 1 [hp_X]/51.7 g; CHAMOMILE 1 [hp_X]/51.7 g
INACTIVE INGREDIENTS: YELLOW WAX; OLIVE OIL

Nursing Cream

OTC Purpose

Skin Protectant

OTC Active Ingredients

Organic Calendula Officinalis (Calendula) Flower Oil 1X (HPUS)
Organic Chamomilla Recutita (Matricaria) Flower Oil 1X (HPUS)
Organic Althaea Officinalis (Marshmallow) Root 1X (HPUS)

Indications & Usage

■ temporarily protects skin related to ■ nursing ■ pregnancy

■ helps prevent and temporarily protects and helps relieve ■ chapped or cracked nipples

■ temporarily protects and helps relieve minor skin irritation

Warnings

For external use only.

■ Do not use on ■ on deep wounds ■ animal bites ■ serious burns

■ Stop use and ask a doctor if ■ condition worsens ■ symptoms last more than 7 days or clear up and occur again within a few days

■ When using this product keep out of eyes. Rinse with water to remove.

Keep Out of Reach of Children

Storage and Handlin

Store at room temperature.

Dosage & Administration

Clean and dry nipple area before application. Apply as often as needed. Clean and dry nipple area before nursing.

Inactive Ingredients

Organic Olea Europaea (Olive) Fruit Oil, Organic Cera Alba (Beeswax).